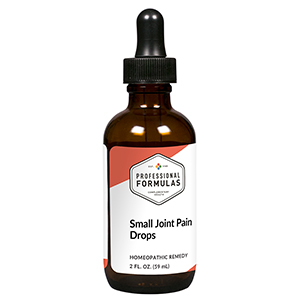 DRUG LABEL: Small Joint Pain Drops
NDC: 63083-2038 | Form: LIQUID
Manufacturer: Professional Complementary Health Formulas
Category: homeopathic | Type: HUMAN OTC DRUG LABEL
Date: 20190815

ACTIVE INGREDIENTS: CALENDULA OFFICINALIS FLOWERING TOP 6 [hp_X]/59 mL; RHODODENDRON AUREUM LEAF 6 [hp_X]/59 mL; RUTA GRAVEOLENS FLOWERING TOP 6 [hp_X]/59 mL; LITHIUM CARBONATE 12 [hp_X]/59 mL; BOVINE TYPE II COLLAGEN (TRACHEAL CARTILAGE) 12 [hp_X]/59 mL; BOS TAURUS LIGAMENT 12 [hp_X]/59 mL; AMMONIUM PHOSPHATE, DIBASIC 12 [hp_X]/59 mL; HYPERICUM PERFORATUM WHOLE 30 [hp_X]/59 mL; SODIUM SULFATE 30 [hp_X]/59 mL; STRYCHNOS NUX-VOMICA SEED 30 [hp_X]/59 mL
INACTIVE INGREDIENTS: ALCOHOL; WATER

C38

ACTIVE INGREDIENTS

Calendula officinalis 6X
Rhododendron chrysanthum 6X
Ruta graveolens 6X
Lithium carbonicum 12X
Cartilage 12X, 30X
Ligament 12X, 30X
Ammonium phosphoricum 12X, 30X, 100X
Hypericum perforatum 30X
Natrum sulphuricum 30X
Nux vomica 30X

QUESTIONS

Professional Formulas

PO Box 2034 Lake Oswego, OR 97035

INDICATIONS

For the temporary relief of minor joint pain or inflammation, particularly in the fingers or toes.*

PURPOSE

*Claims based on traditional homeopathic practice, not accepted medical evidence. Not FDA evaluated.

WARNINGS

In case of overdose, get medical help or contact a poison control center right away.

Keep out of the reach of children.

PREGNANCY OR BREAST FEEDING

If pregnant or breastfeeding, ask a healthcare professional before use.

DIRECTIONS

Place drops under tongue 30 minutes before/after meals. Adults and children 12 years and over: Take 10 drops up to 3 times per day for up to 6 weeks. For immediate onset of symptoms, take 10 to 15 drops every 15 minutes up to 3 hours. For less severe symptoms, take 10-15 drops hourly up to 8 hours. Consult a physician for use in children under 12 years of age.

OTHER INFORMATION

Tamper resistant. If seal is broken, do not use. After opening, close container tightly and store at room temperature away from heat.

INACTIVE INGREDIENTS

20% ethanol, purified water.

LABEL

Est 1985

Professional Formulas

Complementary Health

Small Joint Pain Drops

Homeopathic Remedy

2 FL. OZ. (59 mL)